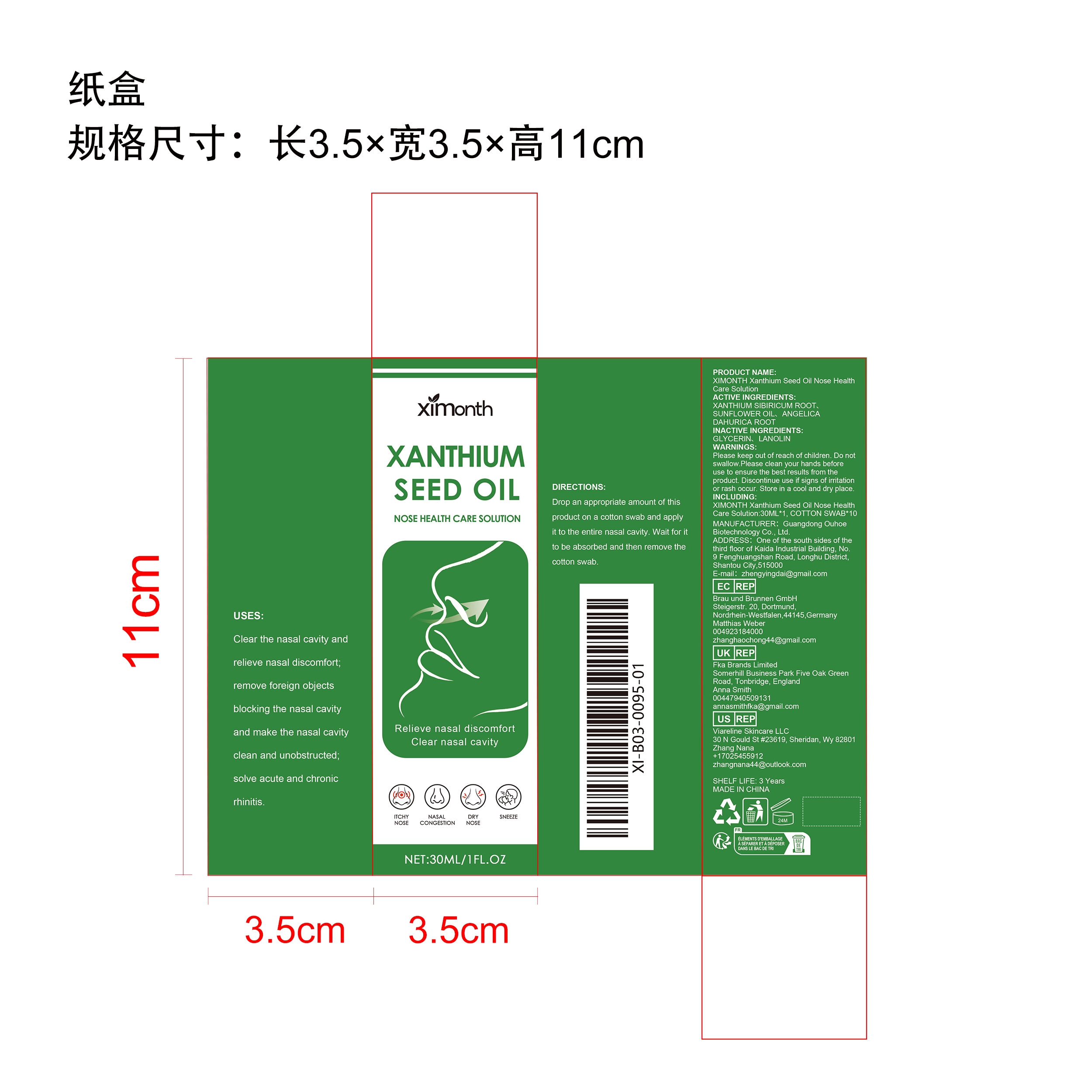 DRUG LABEL: XIMONTH Xanthium Seed Oil Nose Health Care Solution
NDC: 84744-053 | Form: LIQUID
Manufacturer: Guangdong Ouhoe Biotechnology Co., Ltd.
Category: otc | Type: HUMAN OTC DRUG LABEL
Date: 20241022

ACTIVE INGREDIENTS: XANTHIUM SIBIRICUM ROOT 9 mg/30 mg; ANGELICA DAHURICA ROOT 4.5 mg/30 mg; SUNFLOWER OIL 3 mg/30 mg
INACTIVE INGREDIENTS: GLYCERIN 4.5 mg/30 mg; LANOLIN 9 mg/30 mg

ACTIVE INGREDIENTS

XANTHIUM SIBIRICUM ROOT、SUNFLOWER OIL、ANGELICA DAHURICA ROOT

purpose

Clear the nasal cavity andeliee aremove foreign objectsblocking the nasal cavityand make the nasal cavityclean and unobstructed;solve acute and chronicrhinitis.

use

Drop an appropriate amount of this product on a cotton swab and apply it to the entire nasal cavity. Wait for it to be absorbed and then remove the cotton swab.

WARNINGS

Please keep out of reach of children. Do not swallow.Please clean your hands before use to ensure the best results from the product. Discontinue use if signs of irritation or rash occur. Store in a cool and dry place.

Do not use

Discontinue use if signs of irritation or rash occur.

Stop use

Discontinue use if signs of irritation or rash occur.

KEEP OUT OF REACH OF CHILDREN

Please keep out of reach of children. Do not swallow.

STORAGE AND HANDLING

Store in a cool and dry place.

INACTIVE INGREDIENT

GLYCERIN、LANOLIN